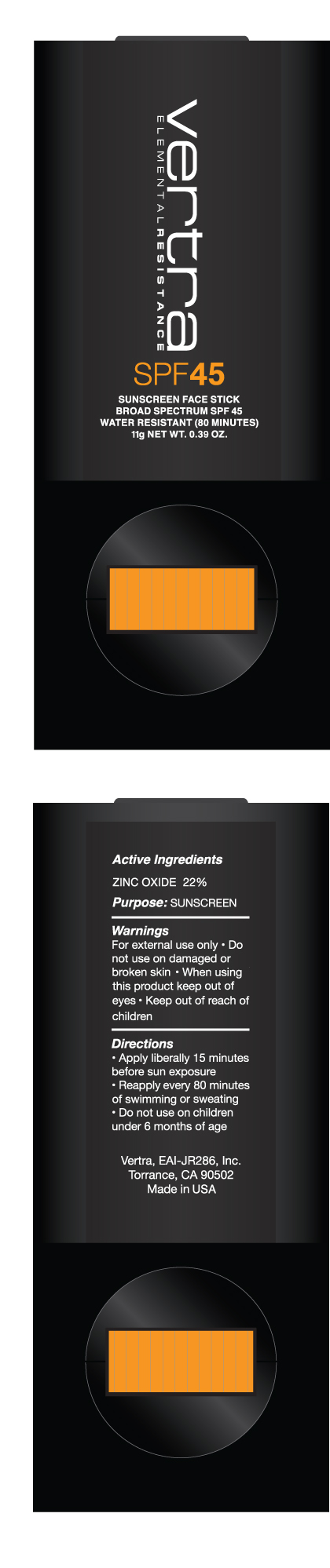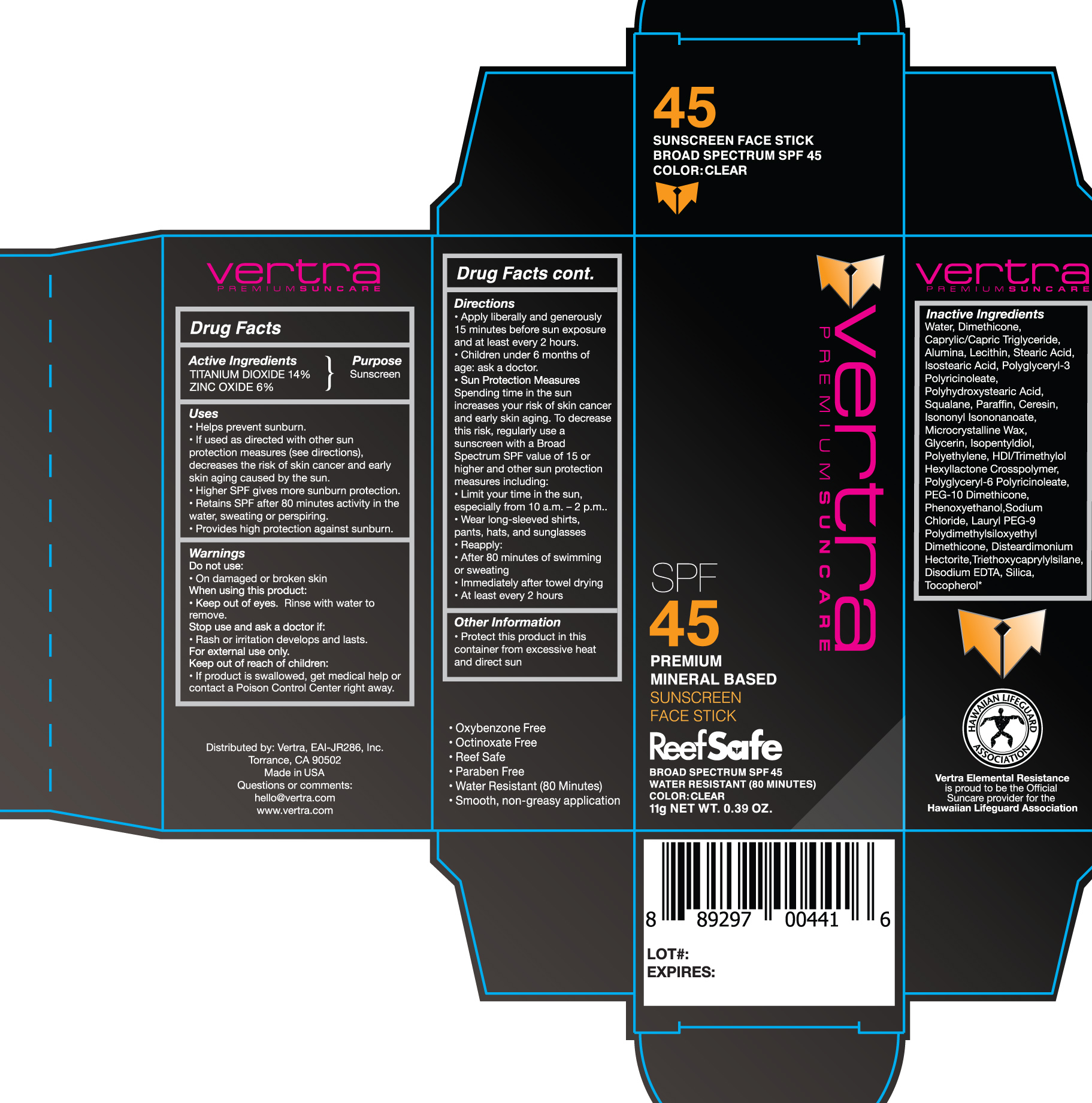 DRUG LABEL: Clear Foundation Sunscreen Broad Spectrum SPF 45
NDC: 71014-012 | Form: STICK
Manufacturer: Eai-jr 286, Inc
Category: otc | Type: HUMAN OTC DRUG LABEL
Date: 20200312

ACTIVE INGREDIENTS: ZINC OXIDE 6 g/100 g; TITANIUM DIOXIDE 14 g/100 g
INACTIVE INGREDIENTS: PARAFFIN; LAURYL PEG-9 POLYDIMETHYLSILOXYETHYL DIMETHICONE; DISTEARDIMONIUM HECTORITE; HEXAMETHYLENE DIISOCYANATE/TRIMETHYLOL HEXYLLACTONE CROSSPOLYMER; MICROCRYSTALLINE WAX; ISOPENTYLDIOL; LOW DENSITY POLYETHYLENE; EDETATE DISODIUM; TOCOPHEROL; POLYHYDROXYSTEARIC ACID (2300 MW); ISOSTEARIC ACID; WATER; MEDIUM-CHAIN TRIGLYCERIDES; ALUMINUM OXIDE; LECITHIN, SOYBEAN; STEARIC ACID; CERESIN; ISONONYL ISONONANOATE; GLYCERIN; PEG-10 DIMETHICONE (600 CST); PHENOXYETHANOL; SODIUM CHLORIDE; TRIETHOXYCAPRYLYLSILANE; SILICON DIOXIDE; SQUALANE

Vertra Clear Foundation Sunscreen Face Stick Broad Spectrum SPF 45

Active Ingredients Purpose

Titanium Dioxide 14% Sunscreen

Zinc Oxide 6% Sunscreen

PURPOSE

- helps prevent sunburn
- if used as directed with other sun protection measures (see Directions), decreases the risk of skin cancer and early skin aging caused by the sun
- Higher SPF gives more sunburn protection
- Retains SPF after 80 minutes activity in the water, sweating, or perspiring.
- Provides high protection against sunburn

Keep out of reach of children:

If product is swallowed, get medical help or contact a Poison Control Center right away.

Warnings

For external use only

Do not use on damaged or broken skin
When using this product: keep out of eyes
Rinse with water to remove

Directions

apply liberally and evenly 15 minutes before sun exposure and and at least every 2 hours
reapply: after 80 minutes of swimming or sweating

children under 6 months of age: ask a doctor

Sun Protection Measures. Spending time in the sun increases your risk of skin cancer and early skin aging. To decrease this risk, regularly use a sunscreen with a Broad Spectrum SPF value 15 or higher and other sun protection measures including:
limit time in the sun, especially from 10 a.m. - 2 p.m.
wear long-sleeve shirts, pants, hats, and sunglasses
immediately after towel drying

Stop use and ask a doctor if:

rash or irritation develops and lasts

Inactive Ingredients

Water, Dimethicone, Caprylic/Capric Triglyceride, Alumina, Lecithin, Stearic Acid, Isostearic Acid, Polyglyceryl-3 Polyricinoleate, Polyhydroxystearic Acid, Squalane, Paraffin, Ceresin, Isononoyl Isononanoate, Microcrystalline Wax, Glycerin, Isopentyldiol, Polyethylene, HDI/Trimethylol Hexyllactone Crosspolymer, Polyglyceryl-6 Polyricinoleate, PEG-10 Dimethicone, Phenxoyethanol, Sodium Chloride, Lauryl PEG-9 Polydimethylsiloxyethyl Dimethicone, Disteardimonium Hectorite, Triethoxycaprylylsilane, Disodium EDTA, Silica, Tocopherol.

PACKAGE LABEL

Vertra Elemental Resistance

Foundation Sunscreen Face Stick

Broad Spectrum SPF 45

Water Resistant (80 Minutes)

Color: Clear

11g NET WT. 0.39